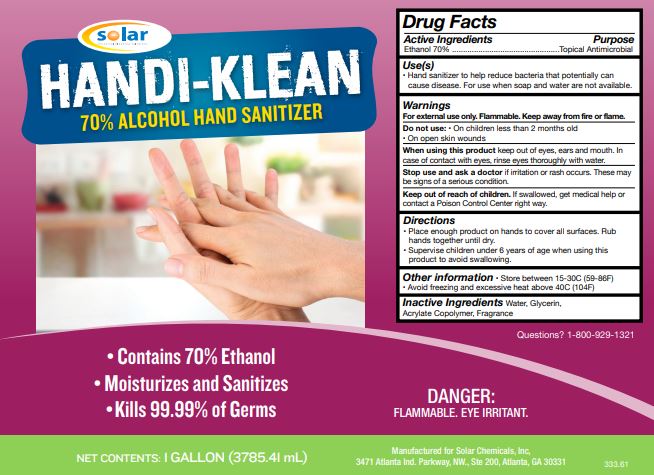 DRUG LABEL: Hand Sanitizer
NDC: 73831-106 | Form: LIQUID
Manufacturer: Solar Chemicals Inc
Category: otc | Type: HUMAN OTC DRUG LABEL
Date: 20200625

ACTIVE INGREDIENTS: ALCOHOL 67.69 mL/100 mL
INACTIVE INGREDIENTS: TROLAMINE 0.175 mL/100 mL; LAVENDER OIL 0.058 mL/100 mL; GLYCERIN 1.776 mL/100 mL; METHACRYLIC ACID - ETHYL ACRYLATE COPOLYMER (4500 MPA.S) 2.225 mL/100 mL; WATER 28.076 mL/100 mL

Handi-Klean 70% Alcohol Hand Sanitizer

Active Ingredient(s)

Ethanol 70% v/v.

Purpose

Topical Antimicrobial

Use

Hand Sanitizer to help reduce bacteria that potentially can cause disease. For use when soap and water are not available.

Warnings

For external use only. Flammable. Keep away from heat or flame

Do not use

- in children less than 2 months of age
- on open skin wounds

When using this product keep out of eyes, ears, and mouth. In case of contact with eyes, rinse eyes thoroughly with water.
Stop use and ask a doctor if irritation or rash occurs. These may be signs of a serious condition.
Keep out of reach of children. If swallowed, get medical help or contact a Poison Control Center right away.

Stop use and ask a doctor if irritation or rash occurs. These may be signs of a serious condition.

Keep out of reach of children. If swallowed, get medical help or contact a Poison Control Center right away.

Directions

- Place enough product on hands to cover all surfaces. Rub hands together until dry.
- Supervise children under 6 years of age when using this product to avoid swallowing.

Other information

- Store between 15-30C (59-86F)
- Avoid freezing and excessive heat above 40C (104F)

Inactive ingredients

water, glycerin, acrylate copolymer, fragrance